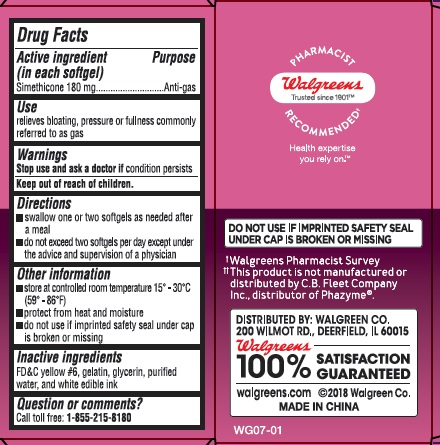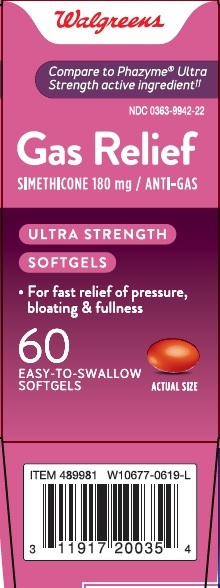 DRUG LABEL: Ultra Strength Gas Relief
NDC: 0363-9942 | Form: CAPSULE, LIQUID FILLED
Manufacturer: Walgreen Co.
Category: otc | Type: HUMAN OTC DRUG LABEL
Date: 20241121

ACTIVE INGREDIENTS: DIMETHICONE 180 mg/1 1
INACTIVE INGREDIENTS: FD&C YELLOW NO. 6; GELATIN; GLYCERIN; WATER

Ultra Strength Gas Relief

Drug Facts

Active ingredient (in each softgel)

Simethicone 180 mg

Purpose

Anti-gas

Uses

- relieves bloating, pressure or fullness commonly referred to as gas

Warnings

Stop use and ask a doctor ifcondition persists

Keep out of reach of children.

Directions

- swallow 1 or 2 softgels as needed after a meal
- do not exceed two softgels per day except under the advice and supervision of a physician

Other information

- store at room temperature 59º - 86ºF (15º - 30ºC)

Inactive ingredients

FD&C yellow#6, gelatin, glycerin, purified water and white edible ink

Questions or comments?

Call toll free: 1-855-215-8180

PRINCIPAL DISPLAY PANEL

Ultra Strength Gas Relief

Simethicone 180 mg Anti-gas 60 Softgels

NDC 0363-9942-22

*Compare to the active ingredient in PHAZYME®Ultra Strength